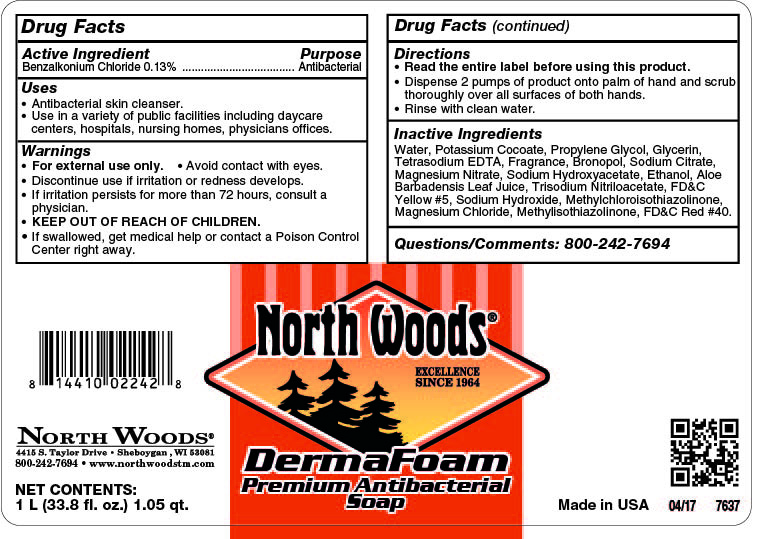 DRUG LABEL: DermaFoam Premium Antibacterial
NDC: 53125-709 | Form: SOAP
Manufacturer: Superior Chemical
Category: otc | Type: HUMAN OTC DRUG LABEL
Date: 20200729

ACTIVE INGREDIENTS: BENZALKONIUM CHLORIDE 0.13 mg/1 mL
INACTIVE INGREDIENTS: FD&C YELLOW NO. 5; WATER; COCAMIDOPROPYLAMINE OXIDE; N-ALKYL DIMETHYL BENZYL AMMONIUM CHLORIDE (C12-C18); GLYCERIN; HYDROGEN PEROXIDE; MAGNESIUM NITRATE; ALCOHOL; ALOE VERA LEAF; METHYLCHLOROISOTHIAZOLINONE; METHYLISOTHIAZOLINONE; FD&C RED NO. 40; GERANIOL; 2-TERT-BUTYLCYCLOHEXYLOXYBUTANOL; ALLYL HEPTANOATE; CITRAL; LIMONENE, (+)-; 2-TERT-BUTYLCYCLOHEXYL ACETATE; TETRASODIUM GLUTAMATE DIACETATE; ANHYDROUS CITRIC ACID; LINALOOL, (+/-)-; DIHYDROMYRCENOL

DermaFoam Premium Antibacterial

DermaFoam Premium Antibacterial Active Ingredients

Active Ingredient

Benzalkonium Chloride 0.13%

DermaFoam Premium Antibacterial Indications

Uses

- Antibacterial skin cleanser.
- Use in a variety of public facilities including daycare centers, hospitals, nursing homes, physicians offices.

DermaFoam Premium Antibacterial Warnings

Warnings

- For external use only.
- Avoid contact with eyes.
- If contact occurs, rinse thoroughly with water.
- Discontinue use is irritation or redness develops.
- If irritation persists for more than 72 hours, consult a physician.
- KEEP OUT OF REACH OF CHILDREN.
- If swallowed, get medical help or contact a Poison Control Center right away.

DermaFoam Premium Antibacterial Dosage

Directions

- Read the entire label before using this product.
- Dispense 2 pumps of product onto palm of hand and scrub thoroughly over all surfaces of both hands.
- Rinse with clean water.

DermaFoam Premium Antibacterial Inactive Ingredients

Inactive Ingredients

Water, Potasium Cocoate, Propylene Glycol, Glycerin, Tetrasodium EDTA, Fragrance, Bronopol, Sodium Citrate, Magnesium Nitrate, Sodium Hydroxyacetate, Ethanol, Aloe Barbadensis Leaf Juice, Trisodium Nitriloacetate, FD&C Yellow #5, Sodium Hydroxide, Methylchloroisothiazolinone, Magnesium Chloride, Methylisothiazolinone, FD&C Red #40.

DermaFoam Premium Antibacterial Purpose

Purpose

Antibacterial

DermaFoam Premium Antibacterial Keep our of Reach of Children

KEEP OUT OF REACH OF CHILDREN

DermaFoam Premium Antibacterial

75129-00_Derma Foam Premium Antibacterial.jpg